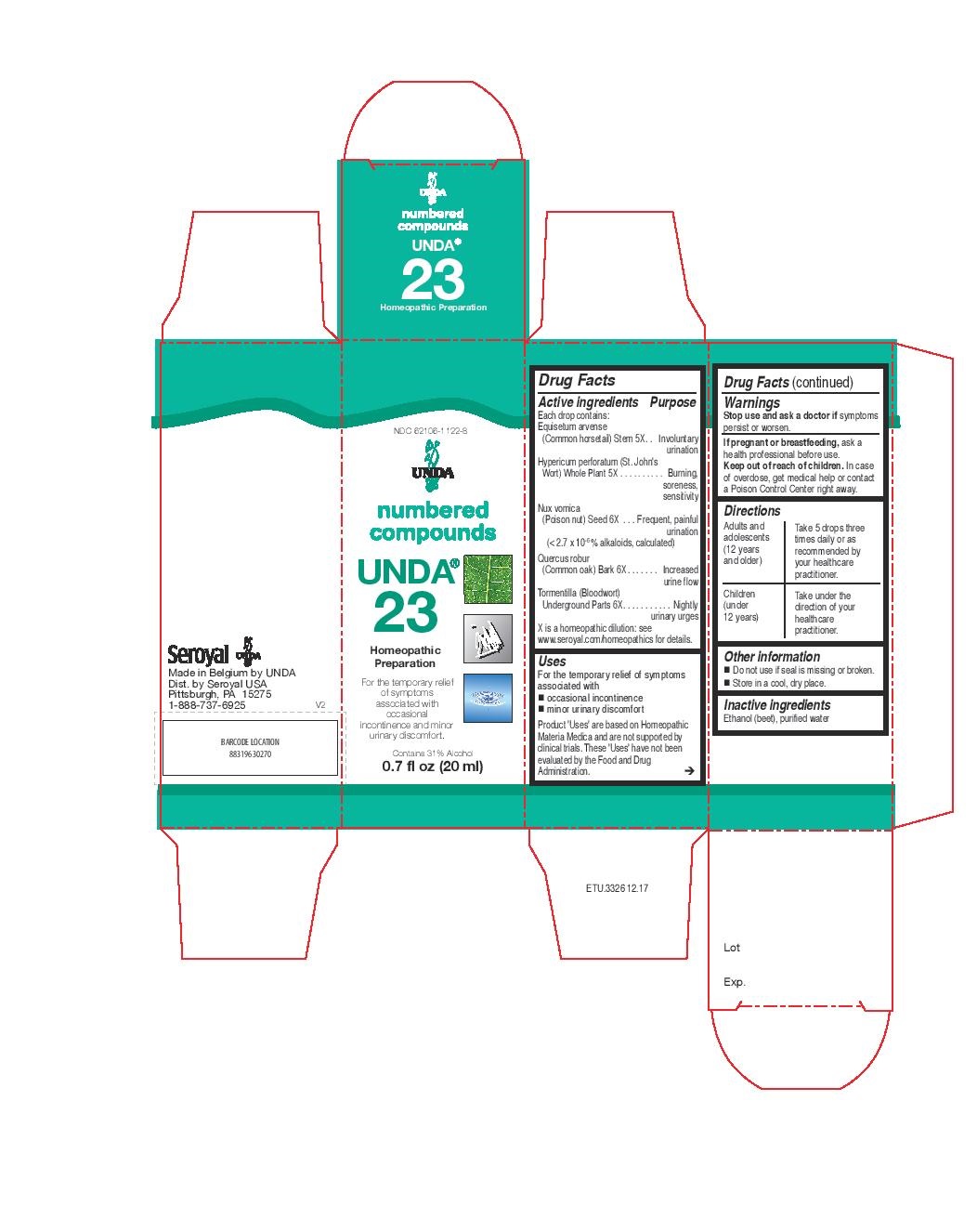 DRUG LABEL: Unda 23
NDC: 62106-1122 | Form: LIQUID
Manufacturer: Seroyal USA
Category: homeopathic | Type: HUMAN OTC DRUG LABEL
Date: 20221109

ACTIVE INGREDIENTS: STRYCHNOS NUX-VOMICA SEED 6 [hp_X]/20 mL; QUERCUS ROBUR TWIG BARK 6 [hp_X]/20 mL; EQUISETUM ARVENSE BRANCH 5 [hp_X]/20 mL; HYPERICUM PERFORATUM 5 [hp_X]/20 mL; POTENTILLA ERECTA ROOT 6 [hp_X]/20 mL
INACTIVE INGREDIENTS: ALCOHOL; WATER

Unda 23

Active ingredients

Each drop contains:
Equisetum arvense (Common horsetail) Stem 5X
Hypericum perforatum (St. John's Wort) Whole Plant 5X
Nux vomica (Poison nut) Seed 6X (< 2.7 x 10-6 % alkaloids, calculated)
Quercus robur (Common oak) Bark 6X
Tormentilla (Bloodwort) Underground Parts 6X

Uses
For the temporary relief of symptoms associated with
occasional incontinence
minor urinary discomfort

Warnings
Stop use and ask a doctor if symptoms persist or worsen.
If pregnant or breastfeeding, ask a health professional before use.
Keep out of reach of children.

In case of overdose, get medical help or contact a Poison Control Center right away.

Stop use and ask a doctor if symptoms persist or worsen.

PREGNANCY OR BREAST FEEDING

If pregnant or breastfeeding, ask a health professional before use.

Keep out of reach of children.

OVERDOSAGE

In case of overdose, get medical help or contact a Poison Control Center right away.

Inactive ingredients
Ethanol (beet), purified water

Other information
Do not use if seal is missing or broken.
Store in a cool, dry place.

Directions
Adults and adolescents (12 years and older)

Take 5 drops three times daily or as recommended by your healthcare practitioner.

Children (under 12 years)

Take under the direction of your healthcare practitioner.

Uses
For the temporary relief of symptoms associated with
occasional incontinence
minor urinary discomfort

Directions
Adults and adolescents (12 years and older)

Take 5 drops three times daily or as recommended by your healthcare practitioner.

Children (under 12 years)

Take under the direction of your healthcare practitioner.

PACKAGE LABEL

NDC 62106-1122-8

UNDA

numbered compounds

UNDA 23

Homeopathic Preparation

For the temporary relief of symptoms associated

with occasional incontinence and minor urinary discomfort.

Contains 31% Alcohol
0.7 fl oz (20 mL)